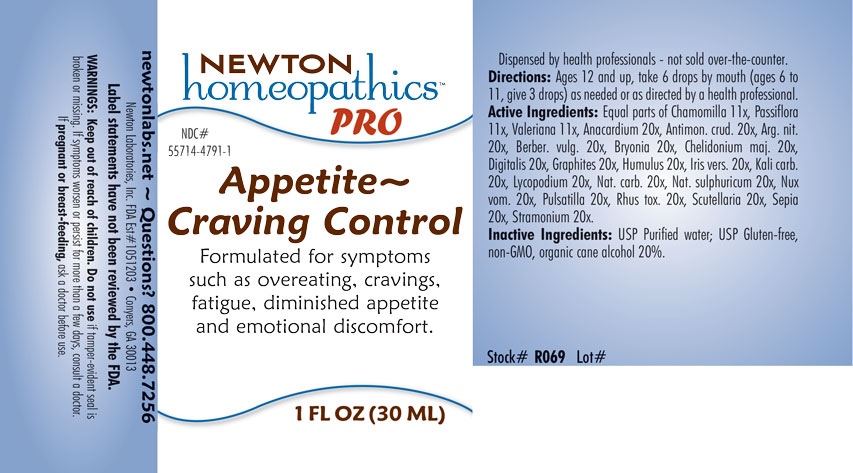 DRUG LABEL: Appetite - Craving Control
NDC: 55714-4791 | Form: LIQUID
Manufacturer: Newton Laboratories, Inc.
Category: homeopathic | Type: HUMAN OTC DRUG LABEL
Date: 20201202

ACTIVE INGREDIENTS: SODIUM SULFATE 20 [hp_X]/1 mL; SEPIA OFFICINALIS JUICE 20 [hp_X]/1 mL; HOPS 20 [hp_X]/1 mL; SODIUM CARBONATE 20 [hp_X]/1 mL; TOXICODENDRON PUBESCENS LEAF 20 [hp_X]/1 mL; SCUTELLARIA LATERIFLORA WHOLE 20 [hp_X]/1 mL; SILVER NITRATE 20 [hp_X]/1 mL; CHELIDONIUM MAJUS 20 [hp_X]/1 mL; GRAPHITE 20 [hp_X]/1 mL; IRIS VERSICOLOR ROOT 20 [hp_X]/1 mL; PASSIFLORA INCARNATA FLOWERING TOP 11 [hp_X]/1 mL; DIGITALIS 20 [hp_X]/1 mL; VALERIAN 11 [hp_X]/1 mL; SEMECARPUS ANACARDIUM JUICE 20 [hp_X]/1 mL; ANTIMONY TRISULFIDE 20 [hp_X]/1 mL; MATRICARIA CHAMOMILLA 11 [hp_X]/1 mL; BERBERIS VULGARIS ROOT BARK 20 [hp_X]/1 mL; BRYONIA ALBA ROOT 20 [hp_X]/1 mL; POTASSIUM CARBONATE 20 [hp_X]/1 mL; LYCOPODIUM CLAVATUM SPORE 20 [hp_X]/1 mL; STRYCHNOS NUX-VOMICA SEED 20 [hp_X]/1 mL; ANEMONE PULSATILLA 20 [hp_X]/1 mL; DATURA STRAMONIUM 20 [hp_X]/1 mL
INACTIVE INGREDIENTS: WATER; ALCOHOL

Appetite 4791L

INDICATIONS & USAGE SECTION

Formulated for symptoms such as overeating, cravings, fatigue, diminished appetite and emotional discomfort.

DOSAGE & ADMINISTRATION SECTION

Directions: Ages 12 and up, take 6 drops by mouth (ages 0 to 11, give 3 drops) one to four times daily or as directed by a health professional.

OTC - ACTIVE INGREDIENT SECTION

Equal parts of Chamomilla 11x, Passiflora 11x, Valeriana 11x, Anacardium 20x, Antimon. crud. 20x, Arg. nit. 20x, Berber. vulg. 20x, Bryonia 20x, Chelidonium maj. 20x, Digitalis 20x, Graphites 20x, Humulus 20x, Iris vers. 20x, Kali carb. 20x, Lycopodium 20x, Nat. carb. 20x, Nat. sulphuricum 20x, Nux vom. 20x, Pulsatilla 20x, Rhus tox. 20x, Scutellaria 20x, Sepia 20x, Stramonium 20x

OTC - PURPOSE SECTION

Formulated for symptoms such as overeating, cravings, fatigue, diminished appetite and emotional discomfort.

INACTIVE INGREDIENT SECTION

Inactive Ingredients: USP Purified Water; USP Gluten-free, non-GMO, organic cane alcohol 20%.

QUESTIONS SECTION

newtonlabs.net - Questions? 800.448.7256

Newton Laboratories, Inc. FDA Est # 1051203 Conyers, GA 30013

WARNINGS SECTION

WARNINGS: Keep out of reach of children. Do not use if tamper-evident seal is broken or missing. If symptoms or persist for more than a few days, consult a doctor. If pregnant or breast-feeding, ask a doctor before use.

OTC - PREGANCY OR BREAST FEEDING SECTION

If pregnant or breast-feeding, ask a doctor before use.

OTC - KEEP OUT OF REACH OF CHILDREN SECTION

Keep out of reach of children.